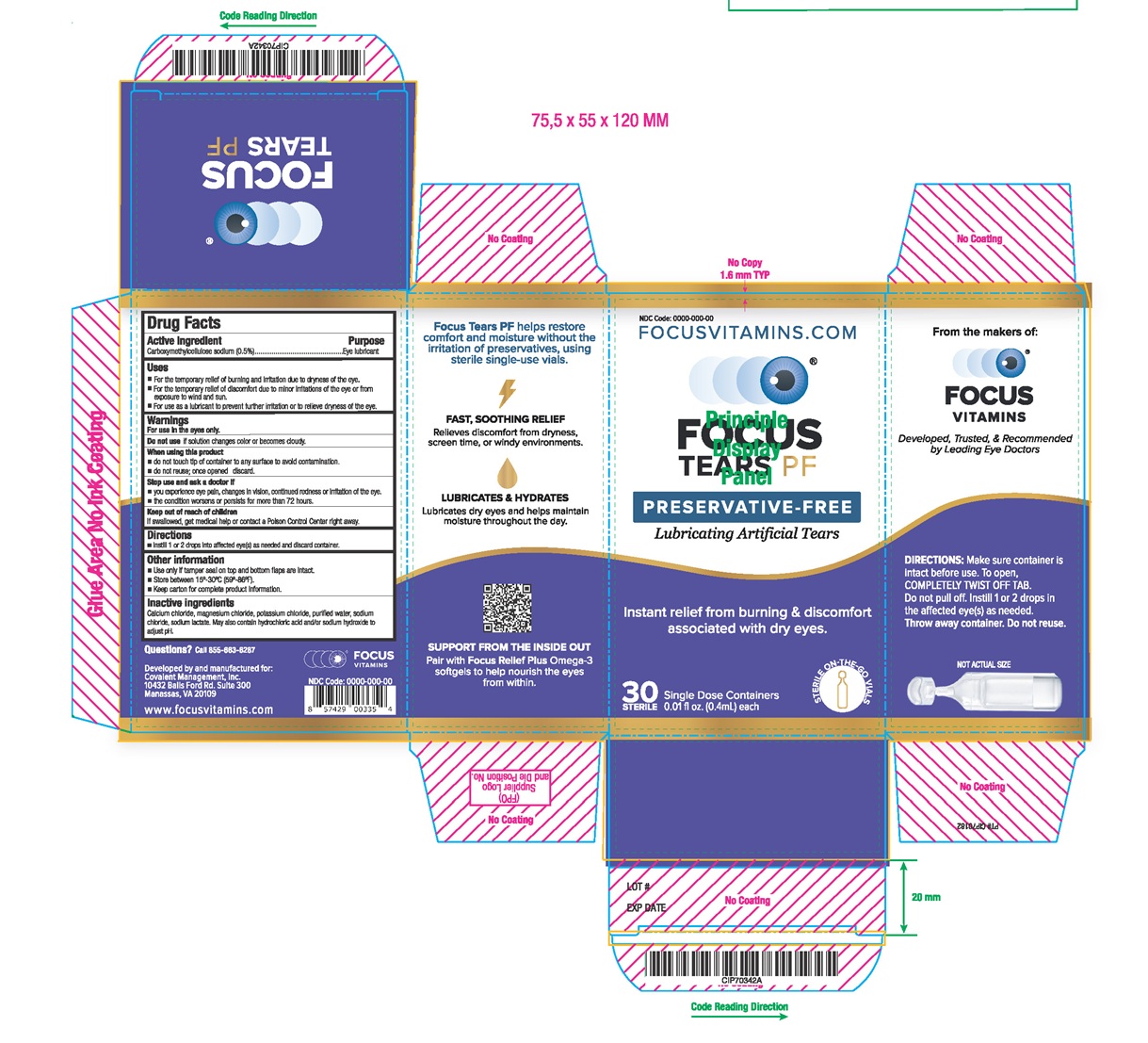 DRUG LABEL: Focus Tears PF
NDC: 82724-009 | Form: SOLUTION/ DROPS
Manufacturer: Covalent Medical
Category: otc | Type: HUMAN OTC DRUG LABEL
Date: 20250717

ACTIVE INGREDIENTS: CARBOXYMETHYLCELLULOSE SODIUM 5 mg/1 mL
INACTIVE INGREDIENTS: CALCIUM CHLORIDE; MAGNESIUM CHLORIDE; POTASSIUM CHLORIDE; WATER; SODIUM CHLORIDE; SODIUM LACTATE; HYDROCHLORIC ACID; SODIUM HYDROXIDE

Carboxymethylcellulose sodium

Active ingredient

Carboxymethylcellulose sodium (0.5%)

Purpose

Eye Lubricant

Warnings

For use in the eyes only.

When using this product

■ do not touch tip of container to any surface to avoid contamination.
■ do not reuse; once opened discard.

Stop use and ask a doctor if

■ you experience eye pain, changes in vision, continued redness or irritation of the eye.
■ tile condition worsens or persists for more than 72 hours.

Keep out of reach of children

If swallowed, get medical help or contact a Poison Control Center right away.

Directions

■ Instill 1 or 2 drops into affected eye(s) as needed and discard container.

Other information

■ Use only if tamper seal on top and bottom flaps are intact.
■ Store between 15°-30°C (59°-86°F).
■ Keep carton for complete product information.

Inactive ingredients

Calcium chloride, magnesium chloride, potassium chloride, purified water, sodium chloride, sodium lactate. May also contain hydrochloric acid and/or sodium hydroxide to adjust pH.

PACKAGE LABEL

Principal Display Panel